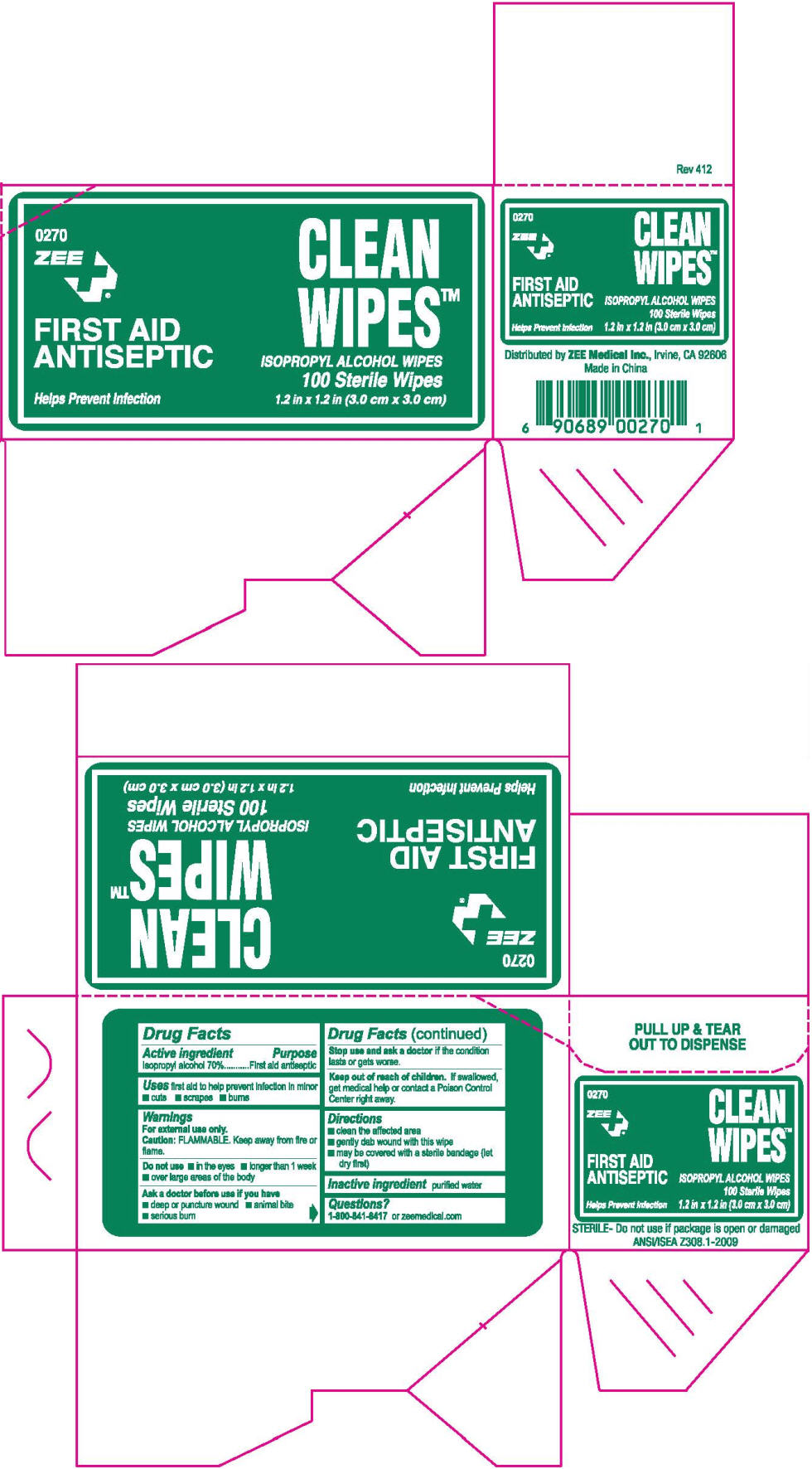 DRUG LABEL: Alcohol  Prep pad
NDC: 35418-203 | Form: SWAB
Manufacturer: ZEE MEDICAL
Category: otc | Type: HUMAN OTC DRUG LABEL
Date: 20130116

ACTIVE INGREDIENTS: Isopropyl Alcohol 0.7 mL/1 mL
INACTIVE INGREDIENTS: water

Alcohol Prep pad

Drug Facts

Active ingredient

Isopropyl alcohol 70%

Purpose

First aid antiseptic

Uses

first aid to help prevent infection in minor

- cuts
- scrapes
- burns

Warnings

For external use only.

Caution

FLAMMABLE. Keep away from fire or flame.

Do not use

- in the eyes
- longer than 1 week
- over large areas of the body

Ask a doctor before use if you have

- deep or puncture wound
- animal bite
- serious burn

Stop use and ask a doctor if the condition lasts or gets worse.

Keep out of reach of children. If swallowed, get medical help or contact a Poison Control Center right away.

Directions

- clean the affected area
- gently dab wound with this wipe
- may be covered with a sterile bandage (let dry first)

Inactive ingredient

purified water

Questions?

1-800-841-8417 or zeemedical.com

Distributed byZEE Medical Inc., Irvine, CA 92606

PRINCIPAL DISPLAY PANEL - 100 Wipe Carton

0270

ZEE

FIRST AID
ANTISEPTIC

Helps Prevent Infection

CLEAN
WIPES™

ISOPROPYL ALCOHOL WIPES
100 Sterile Wipes
1.2 in x 1.2 in (3.0 cm x 3.0 cm)